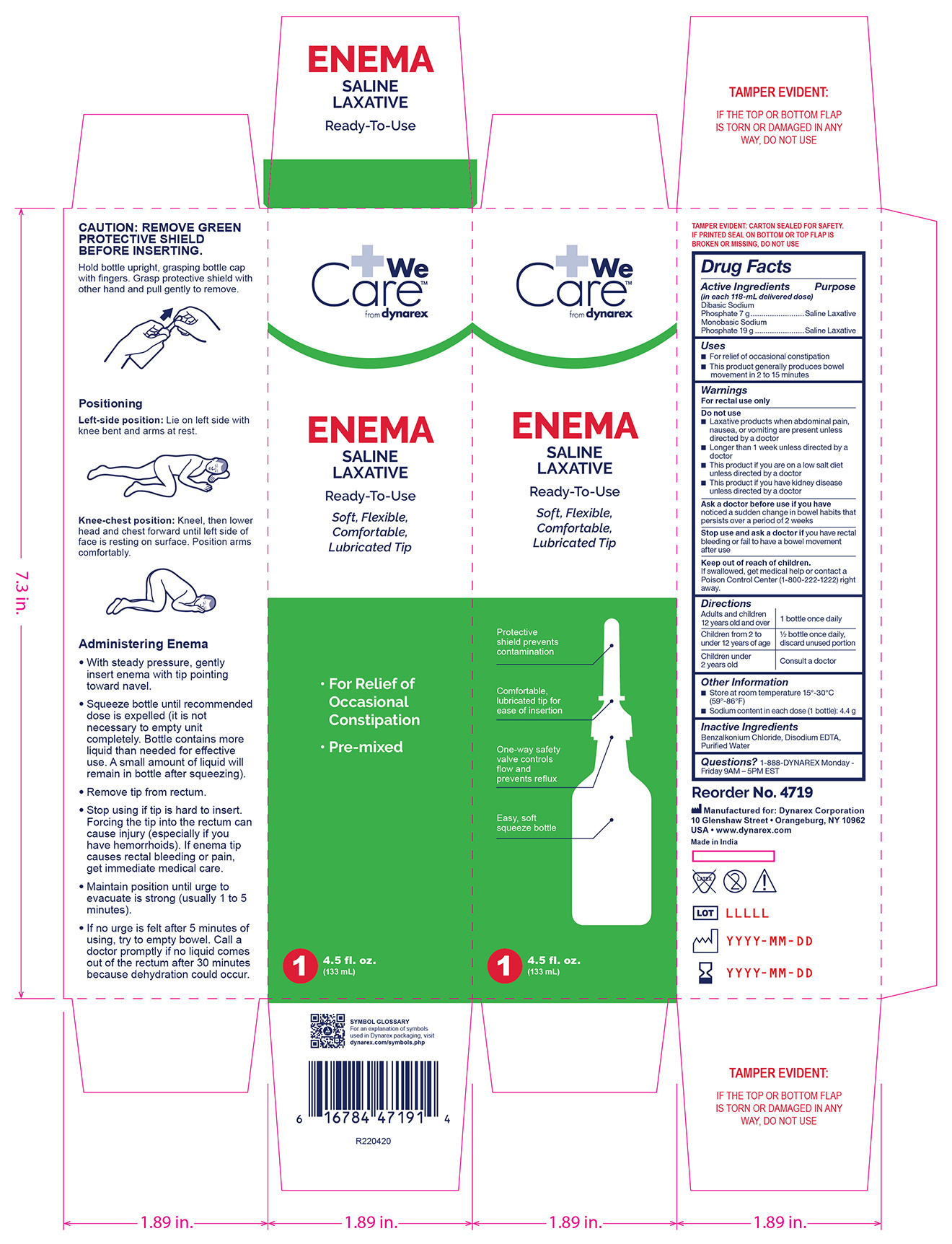 DRUG LABEL: Saline Enema
NDC: 67777-402 | Form: ENEMA
Manufacturer: Dynarex Corporation
Category: otc | Type: HUMAN OTC DRUG LABEL
Date: 20250514

ACTIVE INGREDIENTS: SODIUM PHOSPHATE, DIBASIC 7 g/118 mL; SODIUM PHOSPHATE, MONOBASIC 19 g/118 mL
INACTIVE INGREDIENTS: BENZALKONIUM CHLORIDE; WATER; EDETATE DISODIUM ANHYDROUS

4719 Enema, Saline NDC 67777-402-01

Active Ingredients

(in each 118 mL delivered dose)

Dibasic Sodium Phosphate 7g

Monobasic Sodium Phosphate 19g

Purpose

Saline Laxative

Uses

• For relief of occasional constipation

• This product generally produces bowel movement in 2 to 15 minutes

Warnings:

For rectal use only

Dosage Warning: Using more than one enema in 24 hours can be harmful.

Do not use

• Laxative products when abdominal pain, nausea, or vomiting are present unless directed by a doctor

• Longer than 1 week unless directed by a doctor

• This product if you are on a low salt diet unless directed by a doctor

• This product if you have kidney disease unless directed by a doctor

Ask a doctor before use if you have:

Noticed a sudden change in bowel habits that persists over a period of 2 weeks

Stop use and ask a doctor if:

- If you have rectal bleeding or fail to have a bowel movement after use

Keep out of reach of children

If swallowed, get medical help or contact a Poison Control Center (1-800-222-1222) right away.

Directions

Adults and children 12 years old and over - 1 bottle once daily

Children 2 to under 12 years of age - 1/2 bottle once daily, discard unused portion

Children under 2 years - Consult a physician.

Other information:

- Sodium content in each dose (1 bottle): 4.4 g
- Store at room temperature 15º-30ºC (59º- 8ºF)

Inactive ingredients

Benzalkonium Chloride, Disodium EDTA, Purified Water

Questions?

1-888-DYNAREX Monday - Friday 9AM - 5PM EST

Label

4719 Enema Saline Laxative